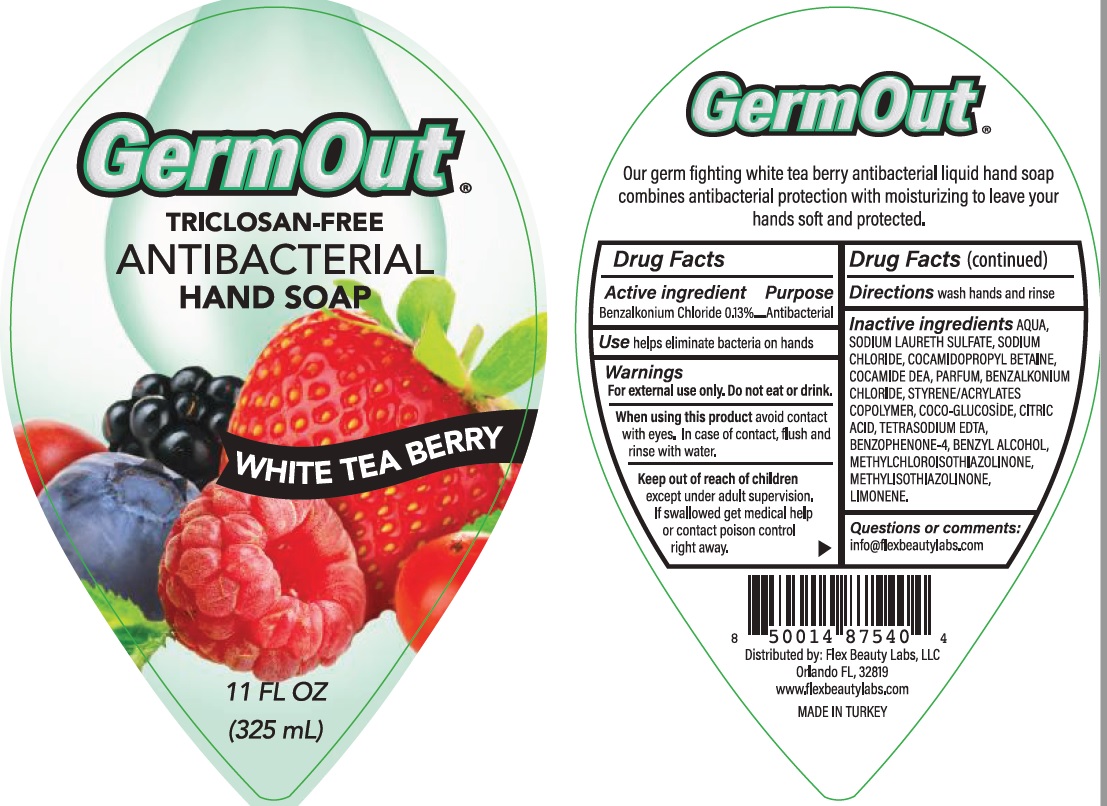 DRUG LABEL: Antibacterial
NDC: 78242-005 | Form: LIQUID
Manufacturer: DIAMO KOZMETIK SANAYI IC VE DIS TICARET LIMITED SIRKETI
Category: otc | Type: HUMAN OTC DRUG LABEL
Date: 20200622

ACTIVE INGREDIENTS: BENZALKONIUM CHLORIDE 1.3 mg/1 mL
INACTIVE INGREDIENTS: WATER; SODIUM LAURETH SULFATE; COCAMIDOPROPYL BETAINE; COCO DIETHANOLAMIDE; SODIUM CHLORIDE; GLYCERIN; DITETRACYCLINE TETRASODIUM EDETATE; METHYLCHLOROISOTHIAZOLINONE; METHYLISOTHIAZOLINONE; SULISOBENZONE; BENZYL ALCOHOL; ANHYDROUS CITRIC ACID; LIMONENE DIEPOXIDE

Antibacterial, Triclosan free- Germout Hand Soap- White Tea Berry

ACTIVE INGREDIENT

Benzalkonium Chloride - 0.13%

Purpose - Antibacterial

INDICATIONS AND USAGE

Use help eliminate bacteria on hands

Warnings For external use only

Causes serious eye damage. Toxic to aquatic life.Avoid release to the environment.

Dispose of contents/container in accordance with national regulations.

Stop use and ask a doctor if irritation or redness develops

When using this product

Avoid contact with eyes.In case of contact, flush and rinse with water.

Remove contact lenses, if present, and easy to do. Continue rinsing.

Keep out of reach of children

Except under adult supervision. DO NOT EAT DRINK.

Keep away from food,drink and animal feeding stuffs,

If swallowed get medical help or contact posion control right away.

Directions

apply onto wet hands.

Lather and rinse thoeoughly.

INACTIVE INGREDIENT

Water, Sodium Laureth Sulfate, Cocamidopropyl Betaine, Sodium Chloride, Citric Acid, Glycerin, Fragrance, Tetrasodium EDTA, Methylchloroisothiazolinone, Methylisothiazolinone, Benzophenone-4,Benzyl Alcohol,Limonene.